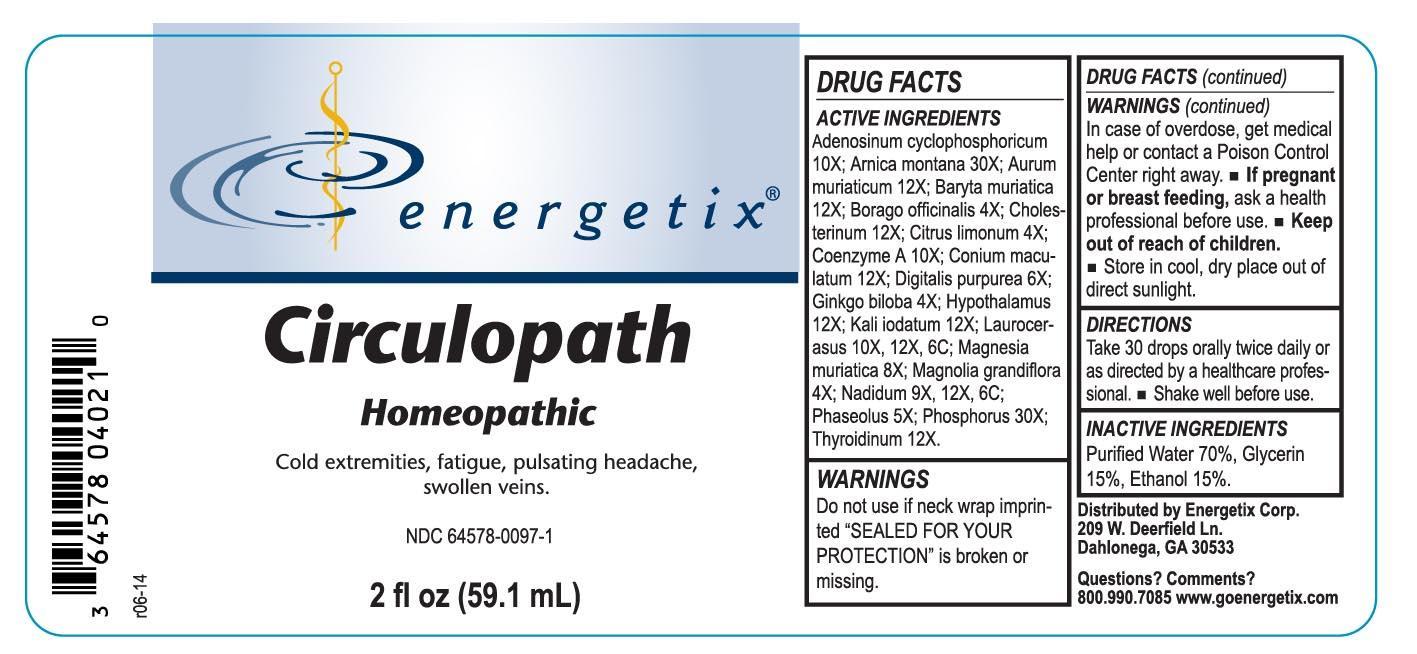 DRUG LABEL: Circulopath
NDC: 64578-0097 | Form: LIQUID
Manufacturer: Energetix Corp
Category: homeopathic | Type: HUMAN PRESCRIPTION DRUG LABEL
Date: 20140207

ACTIVE INGREDIENTS: ADENOSINE CYCLIC PHOSPHATE 10 [hp_X]/59.1 mL; ARNICA MONTANA 30 [hp_X]/59.1 mL; GOLD 12 [hp_X]/59.1 mL; BARIUM CHLORIDE DIHYDRATE 12 [hp_X]/59.1 mL; BORAGE 4 [hp_X]/59.1 mL; CHOLESTEROL 12 [hp_X]/59.1 mL; LEMON JUICE 4 [hp_X]/59.1 mL; COENZYME A 10 [hp_X]/59.1 mL; CONIUM MACULATUM FLOWERING TOP 12 [hp_X]/59.1 mL; DIGITALIS 6 [hp_X]/59.1 mL; GINKGO 4 [hp_X]/59.1 mL; BOS TAURUS HYPOTHALAMUS 12 [hp_X]/59.1 mL; POTASSIUM IODIDE 12 [hp_X]/59.1 mL; PRUNUS LAUROCERASUS LEAF 10 [hp_X]/59.1 mL; MAGNESIUM CHLORIDE 8 [hp_X]/59.1 mL; MAGNOLIA GRANDIFLORA FLOWER 4 [hp_X]/59.1 mL; NADIDE 9 [hp_X]/59.1 mL; KIDNEY BEAN 5 [hp_X]/59.1 mL; PHOSPHORUS 30 [hp_X]/59.1 mL; THYROID, UNSPECIFIED 12 [hp_X]/59.1 mL
INACTIVE INGREDIENTS: WATER 41.356 mL/59.1 mL; ALCOHOL 8.86 mL/59.1 mL; GLYCERIN 8.86 mL/59.1 mL

Circulopath

ACTIVE INGREDIENT

Adenosinum cyclophosphoricum 10X; Arnica montana 30X; Aurum muriaticum 12X; Baryta muriatica 12X; Borago officinalis 4X; Cholesterinum 12X; Citrus limonum 4X; Coenzyme A 10X; Conium maculatum 12X; Digitalis purpurea 6X; Ginkgo biloba 4X; Hypothalamus 12X; Kali iodatum 12X; Laurocerasus 10X, 12X, 6C; Magnesia muriatica 8X; Magnolia grandiflora 4X; Nadidum 9X, 12X, 6C; Phaseolus 5X; Phosphorus 30X; Thyroidinum 12X.

Do not use if neck wrap imprinted "SEALED FOR YOUR PROTECTION" is broken or missing.

OVERDOSAGE

In case of overdose, get medical help or contact a Poison Control Center right away.

PREGNANCY OR BREAST FEEDING

If pregnant or breast feeding, ask a health professional before use.

Keep out of reach of children.

STORAGE AND HANDLING

Store in cool, dry place out of direct sunlight.

Questions? Comments?

800.990.7085 www.goenergetix.com

PURPOSE

Cold extremities, fatigue, pulsating headache, swollen veins.

INACTIVE INGREDIENT

Purified Water 70%, Glycerin 15%, Ethanol 15%.

DOSAGE AND ADMINISTRATION

Take 30 drops orally twice daily or as directed by a healthcare professional. Shake well before use.

INDICATIONS AND USAGE

Cold extremities, fatigue, pulsating headache, swollen veins.